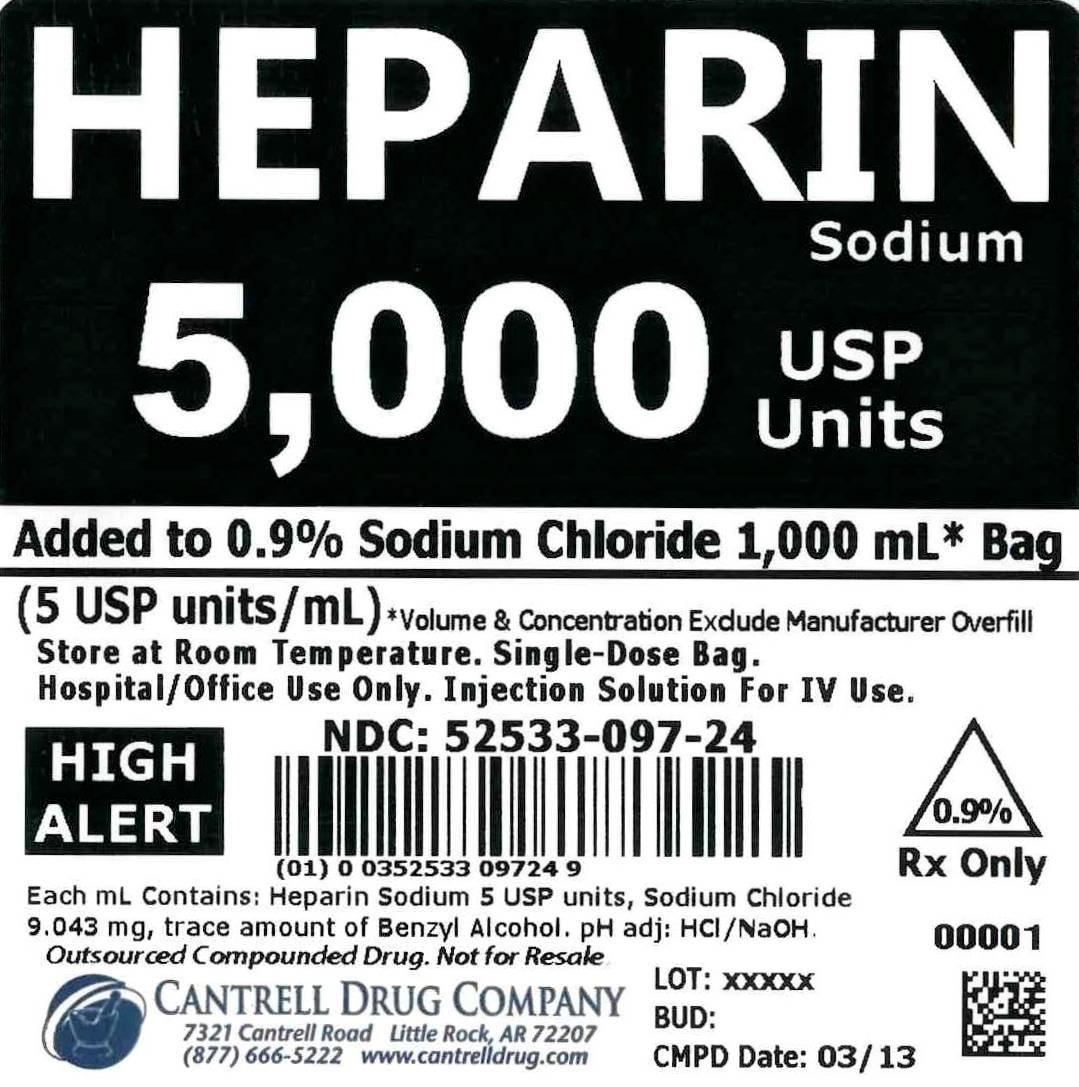 DRUG LABEL: Heparin Sodium
NDC: 52533-097 | Form: INJECTION, SOLUTION
Manufacturer: Cantrell Drug Company
Category: prescription | Type: HUMAN PRESCRIPTION DRUG LABEL
Date: 20150112

ACTIVE INGREDIENTS: Heparin Sodium 5 [USP'U]/1 mL
INACTIVE INGREDIENTS: Sodium Chloride 9 mg/1 mL; BENZYL ALCOHOL 0.00005 mL/1 mL; Water

Heparin Sodium 5,000 USP Units Added to 0.9% Sodium Chloride 1,000 mL Bag